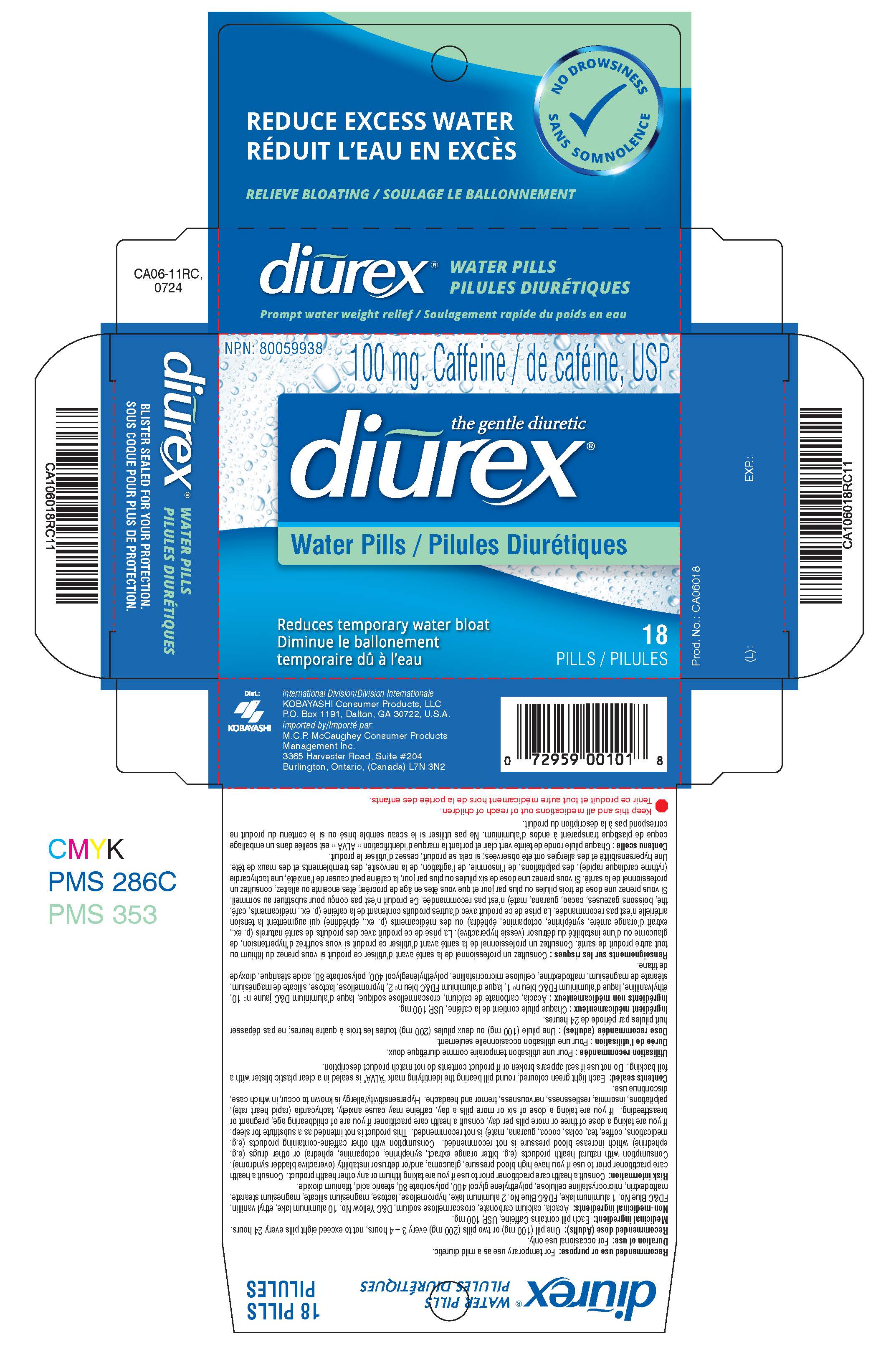 DRUG LABEL: Diurex Water Pills
NDC: 52389-506 | Form: TABLET, FILM COATED
Manufacturer: Kobayashi Healthcare International, Inc.
Category: otc | Type: HUMAN OTC DRUG LABEL
Date: 20250507

ACTIVE INGREDIENTS: CAFFEINE 100 mg/1 1
INACTIVE INGREDIENTS: CALCIUM CARBONATE; ACACIA; CROSCARMELLOSE SODIUM; ETHYL VANILLIN; D&C YELLOW NO. 10; FD&C BLUE NO. 1; FD&C BLUE NO. 2; HYPROMELLOSES; TALC; MAGNESIUM STEARATE; MALTODEXTRIN; CELLULOSE, MICROCRYSTALLINE; POLYETHYLENE GLYCOL 400; POLYSORBATE 80; STEARIC ACID; TITANIUM DIOXIDE; LACTOSE MONOHYDRATE

Canadian Diurex Water Pills